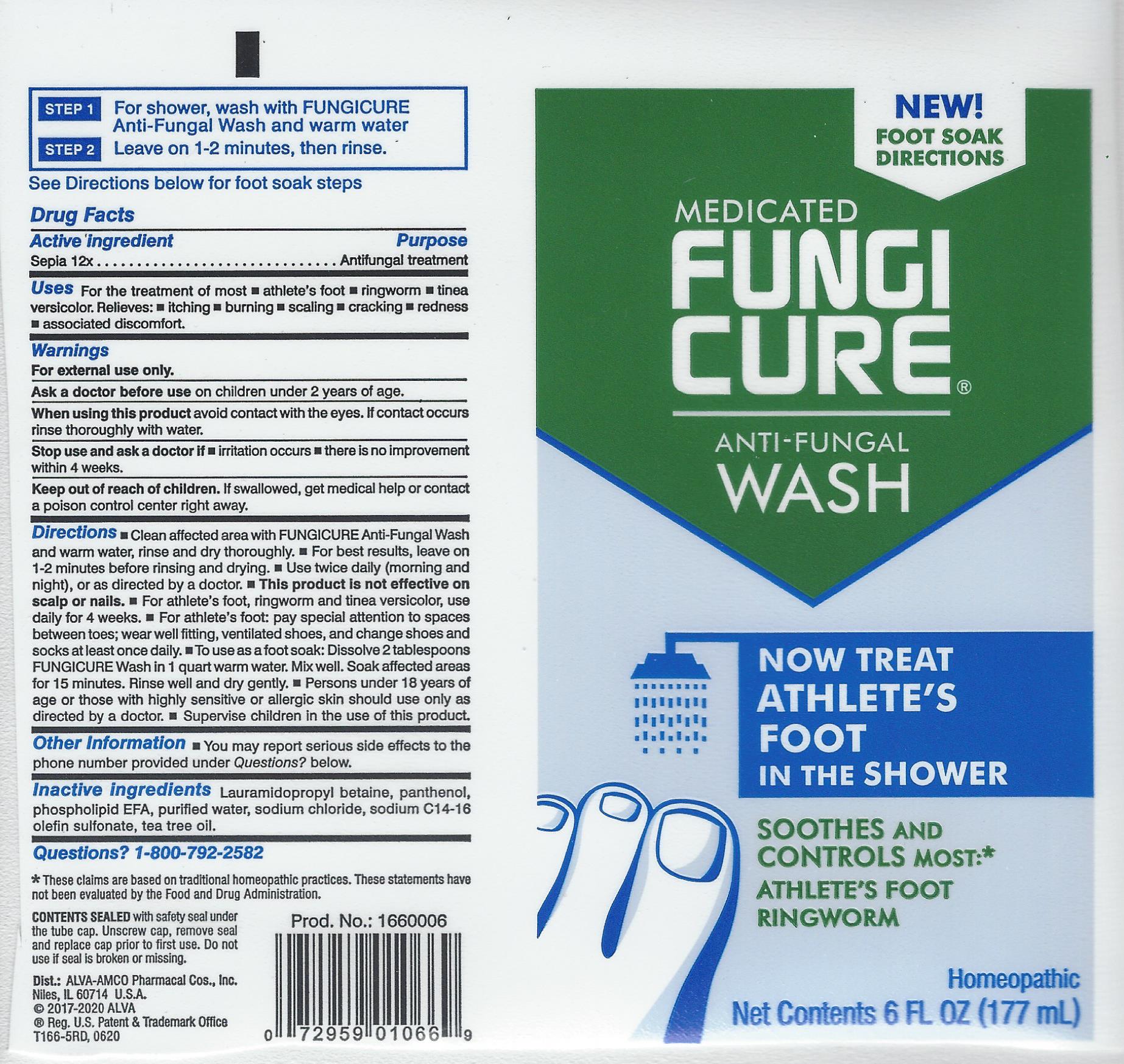 DRUG LABEL: Fungicure
NDC: 52389-666 | Form: SOAP
Manufacturer: Kobayashi Healthcare International, Inc.
Category: homeopathic | Type: HUMAN OTC DRUG LABEL
Date: 20251021

ACTIVE INGREDIENTS: SEPIA OFFICINALIS JUICE 12 [hp_X]/1 mL
INACTIVE INGREDIENTS: LAURAMIDOPROPYL BETAINE; PANTHENOL; LECITHIN, SOYBEAN; WATER; SODIUM CHLORIDE; SODIUM C14-16 OLEFIN SULFONATE; TEA TREE OIL

Fungicure Athlete's Foot Wash

Active ingredient

Sepia 12x

Purpose

Antifungal treatment

Uses

For the treatment of most

- athlete's foot (tinea pedis)
- ringworm (tinea corporis)
- tinea versicolor

For relief of:

- itching
- scaling
- cracking
- burning
- redness
- soreness
- irritation
- discomforts which may accompany these conditions.

Warnings

For external use only

Ask a doctor before use on children under 2 years of age.

When using this product avoid contact with the eyes. If contact occurs rinse thoroughly with water.

Stop use and ask a doctor if

- irritation occurs
- there is no improvement within 4 weeks.

Keep out of reach of children. If swallowed, get medical help or contact a poison control center right away.

Directions

- Read all package directions and warnings before use.
- Use only as directed.
- Clean the affected area with Fungicure Anti-Fungal Wash and warm water, rinse and dry thoroughly.
- For best results, leave on for 1-2 minutes before rinsing and drying.
- Use twice daily (morning and night), or as directed by a doctor.
- This product is not effective on scalp or nails.
- For athlete's foot, ringworm and tinea versicolor use daily for 4 weeks. If condition persists longer, consult a doctor.
- For athlete's foot: pay special attention to spaces between toes; wear well-fitting, ventilated shoes, and change shoes and socks at least once daily.
- Intended for use by normally healthy adults only.
- Persons under 18 years of age or those with highly sensitive or allergic skin should use only as directed by a doctor.
- Supervise children in the use of this product.

Other information

You may report serious side effects to the phone number provided under Questions? below.

Inactive ingredients

Lauramidopropyl betaine, panthenol, phospholipid EFA, purified water, sodium chloride, sodium C14 - 16 olefin sulfonate, tea tree oil.

Questions? 1-800-792-2582